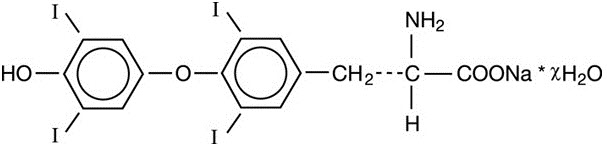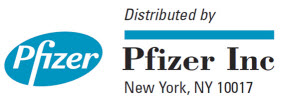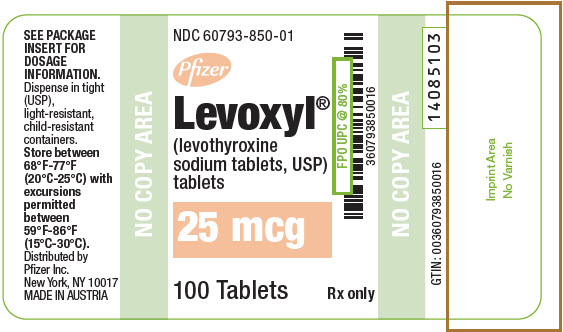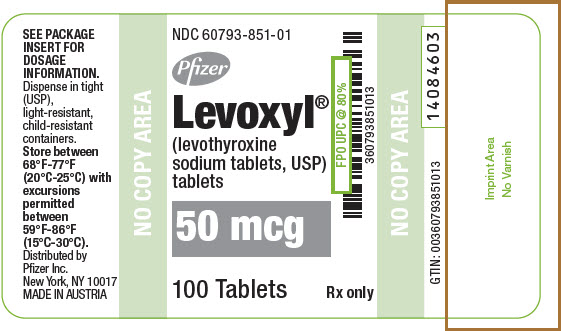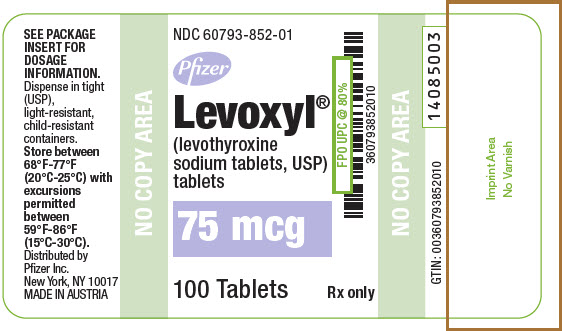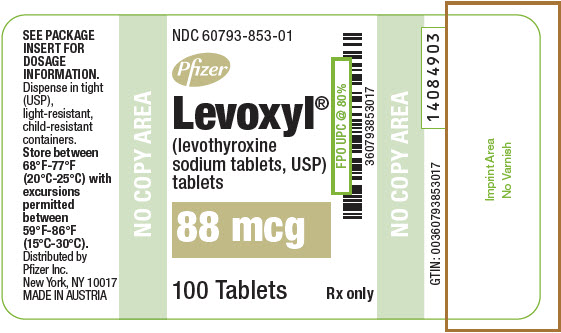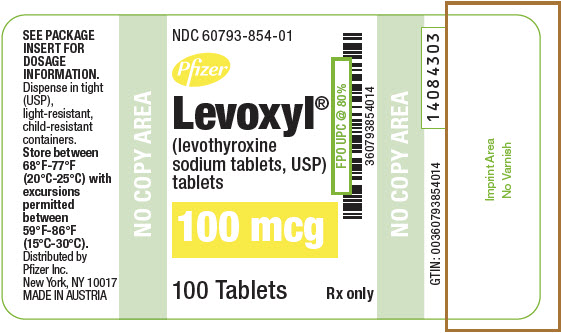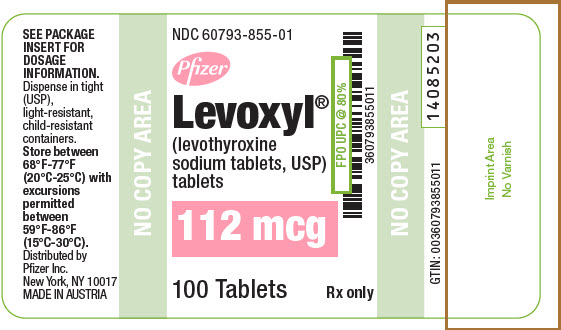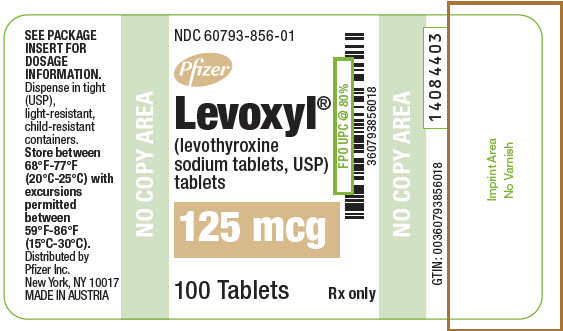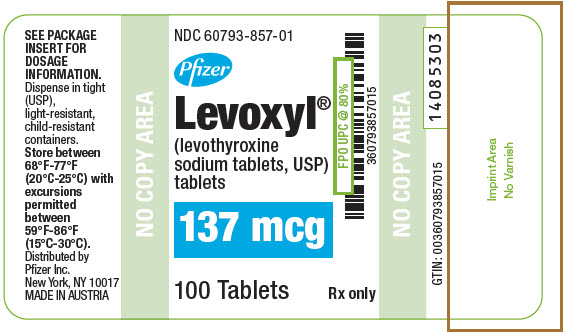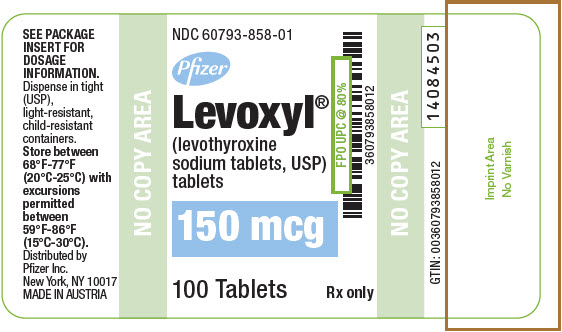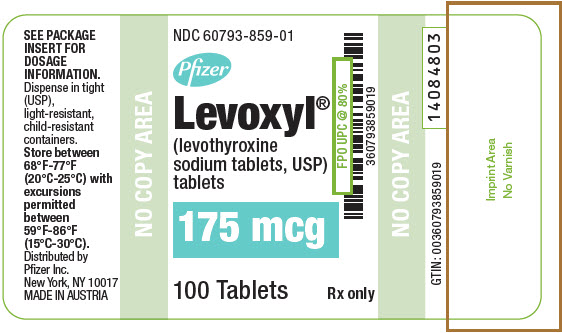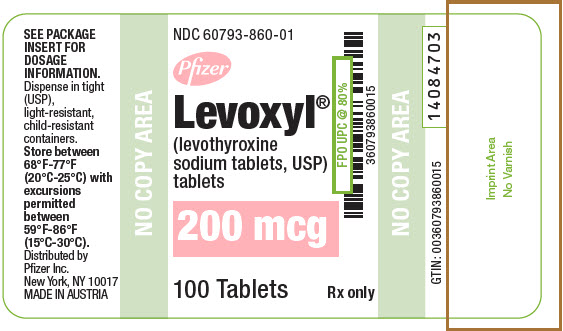 DRUG LABEL: LEVOXYL
NDC: 60793-850 | Form: TABLET
Manufacturer: Pfizer Laboratories Div Pfizer Inc
Category: prescription | Type: HUMAN PRESCRIPTION DRUG LABEL
Date: 20201215

ACTIVE INGREDIENTS: LEVOTHYROXINE SODIUM 25 ug/1 1
INACTIVE INGREDIENTS: SODIUM BICARBONATE; CALCIUM SULFATE DIHYDRATE

HIGHLIGHTS OF PRESCRIBING INFORMATION

These highlights do not include all the information needed to use LEVOXYL safely and effectively. See full prescribing information for LEVOXYL.
LEVOXYL® (levothyroxine sodium) tablets, for oral use
Initial U.S. Approval: 2001

WARNING: NOT FOR TREATMENT OF OBESITY OR FOR WEIGHT LOSS

See full prescribing information for complete boxed warning.

- Thyroid hormones, including LEVOXYL, should not be used for the treatment of obesity or for weight loss.
- Doses beyond the range of daily hormonal requirements may produce serious or even life-threatening manifestations of toxicity (6, 7.7, 10).

1 INDICATIONS AND USAGE

LEVOXYL is L-thyroxine (T4) indicated in pediatric and adult patients for:

- Hypothyroidism: As replacement in primary (thyroidal), secondary (pituitary), and tertiary (hypothalamic) congenital or acquired hypothyroidism. (1)
- Pituitary Thyrotropin (Thyroid-Stimulating Hormone, TSH) suppression: As an adjunct to surgery and radioiodine therapy in the management of well-differentiated thyroid cancer. (1)

Limitations of Use:

- Not indicated for suppression of benign thyroid nodules and nontoxic diffuse goiter in iodine-sufficient patients. (1)
- Not indicated for treatment of hypothyroidism during the recovery phase of subacute thyroiditis. (1)

2 DOSAGE AND ADMINISTRATION

- Administer once daily, on an empty stomach, one-half to one hour before breakfast with a full glass of water. (2.1)
- Administer at least 4 hours before or after drugs that are known to interfere with absorption. (2.1)
- Evaluate the need for dose adjustments when regularly administering within one hour of certain foods that may affect absorption. (2.1)
- Starting dose depends on a variety of factors, including age, body weight, cardiovascular status, concomitant medical conditions (including pregnancy), concomitant medications, co-administered food, and the specific nature of the condition being treated. Peak therapeutic effect may not be attained for 4 to 6 weeks. (2.2)
- See full prescribing information for dosing in specific patient populations. (2.3)
- Adequacy of therapy determined with periodic monitoring of TSH and/or T4 as well as clinical status. (2.4)

3 DOSAGE FORMS AND STRENGTHS

Tablets: 25 mcg, 50 mcg, 75 mcg, 88 mcg, 100 mcg, 112 mcg, 125 mcg, 137 mcg, 150 mcg, 175 mcg, 200 mcg (3)

4 CONTRAINDICATIONS

Uncorrected adrenal insufficiency. (4)

5 WARNINGS AND PRECAUTIONS

- Cardiac adverse reactions in the elderly and in patients with underlying cardiovascular disease: Initiate LEVOXYL at less than the full replacement dose because of the increased risk of cardiac adverse reactions, including atrial fibrillation. (2.3, 5.1, 8.5)
- Myxedema coma: Do not use oral thyroid hormone drug products to treat myxedema coma. (5.2)
- Acute adrenal crisis in patients with concomitant adrenal insufficiency: Treat with replacement glucocorticoids prior to initiation of LEVOXYL treatment. (5.3)
- Prevention of hyperthyroidism or incomplete treatment of hypothyroidism: Proper dose titration and careful monitoring is critical to prevent the persistence of hypothyroidism or the development of hyperthyroidism. (5.4)
- Worsening of diabetic control: Therapy in patients with diabetes mellitus may worsen glycemic control and result in increased antidiabetic agent or insulin requirements. Carefully monitor glycemic control after starting, changing, or discontinuing thyroid hormone therapy. (5.5)
- Decreased bone mineral density associated with thyroid hormone over-replacement: Over-replacement can increase bone resorption and decrease bone mineral density. Give the lowest effective dose. (5.6)

6 ADVERSE REACTIONS

Common adverse reactions for LEVOXYL are primarily those of hyperthyroidism due to therapeutic overdosage: arrhythmias, myocardial infarction, dyspnea, muscle spasm, headache, nervousness, irritability, insomnia, tremors, muscle weakness, increased appetite, weight loss, diarrhea, heat intolerance, menstrual irregularities, and skin rash. (6)

To report SUSPECTED ADVERSE REACTIONS, contact Pfizer, Inc. at 1-800-438-1985 or FDA at 1-800-FDA-1088 or www.fda.gov/medwatch.

7 DRUG INTERACTIONS

See full prescribing information for drugs that affect thyroid hormone pharmacokinetics and metabolism (e.g., absorption, synthesis, secretion, catabolism, protein binding, and target tissue response) and may alter the therapeutic response to LEVOXYL. (7)

8 USE IN SPECIFIC POPULATIONS

Pregnancy may require the use of higher doses of levothyroxine. (2.3, 8.1)

FULL PRESCRIBING INFORMATION

WARNING: NOT FOR TREATMENT OF OBESITY OR FOR WEIGHT LOSS

- Thyroid hormones, including LEVOXYL, either alone or with other therapeutic agents, should not be used for the treatment of obesity or for weight loss.
- In euthyroid patients, doses within the range of daily hormonal requirements are ineffective for weight reduction.
- Larger doses may produce serious or even life-threatening manifestations of toxicity, particularly when given in association with sympathomimetic amines such as those used for their anorectic effects [see Adverse Reactions (6), Drug Interactions (7.7), Overdosage (10)].

1 INDICATIONS AND USAGE

Hypothyroidism

LEVOXYL is indicated in pediatric and adult patients as a replacement therapy in primary (thyroidal), secondary (pituitary), and tertiary (hypothalamic) congenital or acquired hypothyroidism.

Pituitary Thyrotropin (Thyroid-Stimulating Hormone, TSH) Suppression

LEVOXYL is indicated in pediatric and adult patients as an adjunct to surgery and radioiodine therapy in the management of well-differentiated thyroid cancer.

Limitations of Use:

- LEVOXYL is not indicated for suppression of benign thyroid nodules and nontoxic diffuse goiter in iodine-sufficient patients as there are no clinical benefits and overtreatment with LEVOXYL may induce hyperthyroidism [see Warnings and Precautions (5.4)].
- LEVOXYL is not indicated for treatment of hypothyroidism during the recovery phase of subacute thyroiditis.

2 DOSAGE AND ADMINISTRATION

2.1 General Administration Information

Administer LEVOXYL tablets orally as a single daily dose, on an empty stomach, one-half to one hour before breakfast with a full glass of water to avoid choking or gagging [see Adverse Reactions (6)].

Administer LEVOXYL at least 4 hours before or after drugs that are known to interfere with LEVOXYL absorption [see Drug Interactions (7.1)].

Evaluate the need for dose adjustments when regularly administering within one hour of certain foods that may affect LEVOXYL absorption [see Drug Interactions (7.9), Clinical Pharmacology (12.3)].

Administer LEVOXYL to infants and children who cannot swallow intact tablets by crushing the tablet, suspending the freshly crushed tablet in a small amount (5 mL to 10 mL or 1 teaspoon to 2 teaspoons) of water and immediately administering the suspension by spoon or dropper. Do not store the suspension. Do not administer in foods that decrease absorption of LEVOXYL, such as soybean-based infant formula [see Drug Interactions (7.9)].

2.2 General Principles of Dosing

The dose of LEVOXYL for hypothyroidism or pituitary TSH suppression depends on a variety of factors including: the patient's age, body weight, cardiovascular status, concomitant medical conditions (including pregnancy), concomitant medications, co-administered food and the specific nature of the condition being treated [see Dosage and Administration (2.3), Warnings and Precautions (5), Drug Interactions (7)]. Dosing must be individualized to account for these factors and dose adjustments made based on periodic assessment of the patient's clinical response and laboratory parameters [see Dosage and Administration (2.4)].

The peak therapeutic effect of a given dose of LEVOXYL may not be attained for 4 to 6 weeks.

2.3 Dosing in Specific Populations

Primary Hypothyroidism in Adults and in Adolescents in Whom Growth and Puberty Are Complete

Start LEVOXYL at the full replacement dose in otherwise healthy, non-elderly individuals who have been hypothyroid for only a short time (such as a few months). The average full replacement dose of LEVOXYL is approximately 1.6 mcg per kg per day (for example: 100 mcg per day to 125 mcg per day for a 70 kg adult).

Adjust the dose by 12.5 mcg to 25 mcg increments every 4 to 6 weeks until the patient is clinically euthyroid and the serum TSH returns to normal. Doses greater than 200 mcg per day are seldom required. An inadequate response to daily doses of greater than 300 mcg per day is rare and may indicate poor compliance, malabsorption, drug interactions, or a combination of these factors.

For elderly patients or patients with underlying cardiac disease, start with a dose of 12.5 mcg to 25 mcg per day. Increase the dose every 6 to 8 weeks, as needed until the patient is clinically euthyroid and the serum TSH returns to normal. The full replacement dose of LEVOXYL may be less than 1 mcg per kg per day in elderly patients.

In patients with severe longstanding hypothyroidism, start with a dose of 12.5 mcg to 25 mcg per day. Adjust the dose in 12.5 mcg to 25 mcg increments every 2 to 4 weeks until the patient is clinically euthyroid and the serum TSH level is normalized.

Secondary or Tertiary Hypothyroidism

Start LEVOXYL at the full replacement dose in otherwise healthy, non-elderly individuals. Start with a lower dose in elderly patients, patients with underlying cardiovascular disease or patients with severe longstanding hypothyroidism as described above. Serum TSH is not a reliable measure of LEVOXYL dose adequacy in patients with secondary or tertiary hypothyroidism and should not be used to monitor therapy. Use the serum free-T4 level to monitor adequacy of therapy in this patient population. Titrate LEVOXYL dosing per above instructions until the patient is clinically euthyroid and the serum free-T4 level is restored to the upper half of the normal range.

Pediatric Dosage - Congenital or Acquired Hypothyroidism

The recommended daily dose of LEVOXYL in pediatric patients with hypothyroidism is based on body weight and changes with age as described in Table 1. Start LEVOXYL at the full daily dose in most pediatric patients. Start at a lower starting dose in newborns (0 to 3 months) at risk for cardiac failure and in children at risk for hyperactivity (see below). Monitor for clinical and laboratory response [see Dosage and Administration (2.4)].

Table 1: LEVOXYL Dosing Guidelines for Pediatric Hypothyroidism
Age | Daily Dose Per Kg Body Weight [- The dose should be adjusted based on clinical response and laboratory parameters [see Warnings and Precautions (5.4), Drug Interactions (7.10), Use in Specific Populations (8.4)].]
0 to 3 months | 10 mcg/kg daily to 15 mcg/kg daily
3 to 6 months | 8 mcg/kg daily to 10 mcg/kg daily
6 to 12 months | 6 mcg/kg daily to 8 mcg/kg daily
1 to 5 years | 5 mcg/kg daily to 6 mcg/kg daily
6 to 12 years | 4 mcg/kg daily to 5 mcg/kg daily
Greater than 12 years but growth and puberty incomplete | 2 mcg/kg daily to 3 mcg/kg daily
Growth and puberty complete | 1.6 mcg/kg daily

Newborns (0 to 3 months) at Risk for Cardiac Failure:

Consider a lower starting dose in newborns at risk for cardiac failure. Increase the dose every 4 to 6 weeks as needed based on clinical and laboratory response.

Pediatric Patients at Risk for Hyperactivity:

To minimize the risk of hyperactivity in pediatric patients, start at one-fourth the recommended full replacement dose, and increase on a weekly basis by one-fourth the full recommended replacement dose until the full recommended replacement dose is reached.

Pregnancy

Pre-existing Hypothyroidism: LEVOXYL dose requirements may increase during pregnancy. Measure serum TSH and free-T4 as soon as pregnancy is confirmed and, at minimum, during each trimester of pregnancy. In patients with primary hypothyroidism, maintain serum TSH in the trimester-specific reference range. For patients with serum TSH above the normal trimester-specific range, increase the dose of LEVOXYL by 12.5 mcg daily to 25 mcg daily and measure TSH every 4 weeks until a stable LEVOXYL dose is reached and serum TSH is within the normal trimester-specific range. Reduce LEVOXYL dosage to pre-pregnancy levels immediately after delivery and measure serum TSH levels 4 to 8 weeks postpartum to ensure LEVOXYL dose is appropriate.

New Onset Hypothyroidism: Normalize thyroid function as rapidly as possible. In patients with moderate to severe signs and symptoms of hypothyroidism, start LEVOXYL at the full replacement dose (1.6 mcg per kg body weight per day). In patients with mild hypothyroidism (TSH less than 10 mIU per liter) start LEVOXYL at 1 mcg per kg body weight per day. Evaluate serum TSH every 4 weeks and adjust LEVOXYL dosage until a serum TSH is within the normal trimester-specific range [see Use in Specific Populations (8.1)].

TSH Suppression in Well-Differentiated Thyroid Cancer

The dose of LEVOXYL should target TSH levels within the desired therapeutic range. This may require a LEVOXYL dose of greater than 2 mcg per kg per day, depending on the target level for TSH suppression.

2.4 Monitoring TSH and/or Thyroxine (T4) Levels

Assess the adequacy of therapy by periodic assessment of laboratory tests and clinical evaluation. Persistent clinical and laboratory evidence of hypothyroidism despite an apparent adequate replacement dose of LEVOXYL may be evidence of inadequate absorption, poor compliance, drug interactions, or a combination of these factors.

Adults

In adult patients with primary hypothyroidism, monitor serum TSH levels after an interval of 6 to 8 weeks after any change in dose. In patients on a stable and appropriate replacement dose, evaluate clinical and biochemical response every 6 to 12 months and whenever there is a change in the patient's clinical status.

Pediatrics

In patients with congenital hypothyroidism, assess the adequacy of replacement therapy by measuring both serum TSH and total or free-T4. Monitor TSH and total or free-T4 in children as follows: 2 and 4 weeks after the initiation of treatment, 2 weeks after any change in dosage, and then every 3 to 12 months thereafter following dose stabilization until growth is completed. Poor compliance or abnormal values may necessitate more frequent monitoring. Perform routine clinical examination, including assessment of development, mental and physical growth, and bone maturation, at regular intervals.

While the general aim of therapy is to normalize the serum TSH level, TSH may not normalize in some patients due to in utero hypothyroidism causing a resetting of pituitary-thyroid feedback. Failure of the serum T4 to increase into the upper half of the normal range within 2 weeks of initiation of LEVOXYL therapy and/or of the serum TSH to decrease below 20 mIU per liter within 4 weeks may indicate the child is not receiving adequate therapy. Assess compliance, dose of medication administered, and method of administration prior to increasing the dose of LEVOXYL [see Warnings and Precautions (5.4), Use in Specific Populations (8.4)].

Secondary and Tertiary Hypothyroidism

Monitor serum free-T4 levels and maintain in the upper half of the normal range in these patients.

3 DOSAGE FORMS AND STRENGTHS

LEVOXYL tablets are oval, color-coded and, potency marked available as follows:

Strength (mcg) | Color | Tablet Markings
25 | Orange | 25
50 | White | 50
75 | Purple | 75
88 | Olive | 88
100 | Yellow | 100
112 | Rose | 112
125 | Light Brown | 125
137 | Dark Blue | 137
150 | Blue | 150
175 | Turquoise | 175
200 | Pink | 200

4 CONTRAINDICATIONS

Levothyroxine is contraindicated in patients with uncorrected adrenal insufficiency [see Warnings and Precautions (5.3)].

5 WARNINGS AND PRECAUTIONS

5.1 Cardiac Adverse Reactions in the Elderly and in Patients with Underlying Cardiovascular Disease

Overtreatment with levothyroxine may cause an increase in heart rate, cardiac wall thickness, and cardiac contractility and may precipitate angina or arrhythmias, particularly in patients with cardiovascular disease and in elderly patients. Initiate LEVOXYL therapy in this population at lower doses than those recommended in younger individuals or in patients without cardiac disease [see Dosage and Administration (2.3), Use in Specific Populations (8.5)].

Monitor for cardiac arrhythmias during surgical procedures in patients with coronary artery disease receiving suppressive LEVOXYL therapy. Monitor patients receiving concomitant LEVOXYL and sympathomimetic agents for signs and symptoms of coronary insufficiency. If cardiovascular symptoms develop or worsen, reduce or withhold the LEVOXYL dose for one week and restart at a lower dose.

5.2 Myxedema Coma

Myxedema coma is a life-threatening emergency characterized by poor circulation and hypometabolism, and may result in unpredictable absorption of levothyroxine sodium from the gastrointestinal tract. Use of oral thyroid hormone drug products is not recommended to treat myxedema coma. Administer thyroid hormone products formulated for intravenous administration to treat myxedema coma.

5.3 Acute Adrenal Crisis in Patients with Concomitant Adrenal Insufficiency

Thyroid hormone increases metabolic clearance of glucocorticoids. Initiation of thyroid hormone therapy prior to initiating glucocorticoid therapy may precipitate an acute adrenal crisis in patients with adrenal insufficiency. Treat patients with adrenal insufficiency with replacement glucocorticoids prior to initiating treatment with LEVOXYL [see Contraindications (4)].

5.4 Prevention of Hyperthyroidism or Incomplete Treatment of Hypothyroidism

LEVOXYL has a narrow therapeutic index. Over- or undertreatment with LEVOXYL may have negative effects on growth and development, cardiovascular function, bone metabolism, reproductive function, cognitive function, emotional state, gastrointestinal function, and on glucose and lipid metabolism. Titrate the dose of LEVOXYL carefully and monitor response to titration to avoid these effects [see Dosage and Administration (2.4)]. Monitor for the presence of drug or food interactions when using LEVOXYL and adjust the dose as necessary [see Drug Interactions (7), Clinical Pharmacology (12.3)].

5.5 Worsening of Diabetic Control

Addition of levothyroxine therapy in patients with diabetes mellitus may worsen glycemic control and result in increased antidiabetic agent or insulin requirements. Carefully monitor glycemic control after starting, changing, or discontinuing LEVOXYL [see Drug Interactions (7.2)].

5.6 Decreased Bone Mineral Density Associated with Thyroid Hormone Over-Replacement

Increased bone resorption and decreased bone mineral density may occur as a result of levothyroxine over-replacement, particularly in post-menopausal women. The increased bone resorption may be associated with increased serum levels and urinary excretion of calcium and phosphorous, elevations in bone alkaline phosphatase, and suppressed serum parathyroid hormone levels. Administer the minimum dose of LEVOXYL that achieves the desired clinical and biochemical response to mitigate against this risk.

6 ADVERSE REACTIONS

Common adverse reactions with LEVOXYL therapy are primarily those of hyperthyroidism due to therapeutic overdosage [see Warnings and Precautions (5.4), Overdosage (10)]. They include the following:

General: fatigue, increased appetite, weight loss, heat intolerance, fever, excessive sweating

Central nervous system: headache, hyperactivity, nervousness, anxiety, irritability, emotional lability, insomnia

Musculoskeletal: tremors, muscle weakness and cramps

Cardiovascular: palpitations, tachycardia, arrhythmias, increased pulse and blood pressure, heart failure, angina, myocardial infarction, cardiac arrest

Respiratory: dyspnea

Gastrointestinal: diarrhea, vomiting, abdominal cramps, elevations in liver function tests

Dermatologic: hair loss, flushing

Endocrine: decreased bone mineral density

Reproductive: menstrual irregularities, impaired fertility

Seizures have been reported rarely with levothyroxine therapy.

Adverse Reactions in Pediatric Patients

Pseudotumor cerebri and slipped capital femoral epiphysis have been reported in pediatric patients receiving levothyroxine therapy. Overtreatment may result in craniosynostosis in infants and premature closure of the epiphysis in pediatric patients with resultant compromised adult height.

Hypersensitivity Reactions

Hypersensitivity reactions to inactive ingredients have occurred in patients treated with thyroid hormone products. These include urticaria, pruritus, skin rash, flushing, angioedema, various gastrointestinal symptoms (abdominal pain, nausea, vomiting, and diarrhea), fever, arthralgia, serum sickness and wheezing. Hypersensitivity to levothyroxine itself is not known to occur.

Choking and Gagging on LEVOXYL Tablets

There have been reports of choking, gagging, tablet stuck in throat, and dysphagia with LEVOXYL tablets, predominately when LEVOXYL tablets were not taken with water [see Dosage and Administration (2.1)].

7 DRUG INTERACTIONS

7.1 Drugs Known to Affect Thyroid Hormone Pharmacokinetics

Many drugs can exert effects on thyroid hormone pharmacokinetics (e.g., absorption, synthesis, secretion, catabolism, protein binding, and target tissue response) and may alter the therapeutic response to LEVOXYL (see Tables 2 – 5).

Table 2: Drugs That May Decrease T4 Absorption (Hypothyroidism)
Potential impact: Concurrent use may reduce the efficacy of LEVOXYL by binding and delaying or preventing absorption, potentially resulting in hypothyroidism.
Drug or Drug Class | Effect
Calcium Carbonate Ferrous Sulfate | Calcium carbonate may form an insoluble chelate with levothyroxine, and ferrous sulfate likely forms a ferric-thyroxine complex. Administer LEVOXYL at least 4 hours apart from these agents.
Orlistat | Monitor patients treated concomitantly with orlistat and LEVOXYL for changes in thyroid function.
Bile Acid Sequestrants -Colesevelam -Cholestyramine -Colestipol Ion Exchange Resins -Kayexalate -Sevelamer | Bile acid sequestrants and ion exchange resins are known to decrease levothyroxine absorption. Administer LEVOXYL at least 4 hours prior to these drugs or monitor thyroid-stimulating hormone (TSH) levels.
Other drugs: Proton Pump Inhibitors Sucralfate Antacids - Aluminum & Magnesium Hydroxides - Simethicone | Gastric acidity is an essential requirement for adequate absorption of levothyroxine. Sucralfate, antacids and proton pump inhibitors may cause hypochlorhydria, affect intragastric pH, and reduce levothyroxine absorption. Monitor patients appropriately.

Table 3: Drugs That May Alter Thyroxine (T4) and Triiodothyronine (T3) Serum Transport Without Affecting Free Thyroxine (FT4) Concentration (Euthyroidism)
Drug or Drug Class | Effect
Clofibrate Estrogen-containing Oral Contraceptives Estrogens (oral) Heroin/Methadone 5-Fluorouracil Mitotane Tamoxifen | These drugs may increase serum thyroxine-binding globulin (TBG) concentration.
Androgens / Anabolic Steroids Asparaginase Glucocorticoids Slow-Release Nicotinic Acid | These drugs may decrease serum TBG concentration.
Potential impact (below): Administration of these agents with LEVOXYL results in an initial transient increase in FT4. Continued administration results in a decrease in serum T4 and normal FT4 and TSH concentrations.
Salicylates (>2 g/day) | Salicylates inhibit binding of T4 and T3 to TBG and transthyretin. An initial increase in serum FT4 is followed by return of FT4 to normal levels with sustained therapeutic serum salicylate concentrations, although total T4 levels may decrease by as much as 30%.
Other drugs: Carbamazepine Furosemide (>80 mg IV) Heparin Hydantoins Non-Steroidal Anti-inflammatory Drugs - Fenamates | These drugs may cause protein binding site displacement. Furosemide has been shown to inhibit the protein binding of T4 to TBG and albumin, causing an increased free-T4 fraction in serum. Furosemide competes for T4-binding sites on TBG, prealbumin, and albumin, so that a single high dose can acutely lower the total T4 level. Phenytoin and carbamazepine reduce serum protein binding of levothyroxine, and total and FT4 may be reduced by 20% to 40%, but most patients have normal serum TSH levels and are clinically euthyroid. Closely monitor thyroid hormone parameters.

Table 4: Drugs That May Alter Hepatic Metabolism of T4 (Hypothyroidism)
Potential impact: Stimulation of hepatic microsomal drug-metabolizing enzyme activity may cause increased hepatic degradation of levothyroxine, resulting in increased LEVOXYL requirements.
Drug or Drug Class | Effect
Phenobarbital Rifampin | Phenobarbital has been shown to reduce the response to thyroxine. Phenobarbital increases L-thyroxine metabolism by inducing uridine 5'-diphospho-glucuronosyltransferase (UGT) and leads to a lower T4 serum levels. Changes in thyroid status may occur if barbiturates are added or withdrawn from patients being treated for hypothyroidism. Rifampin has been shown to accelerate the metabolism of levothyroxine.

Table 5: Drugs That May Decrease Conversion of T4 to T3
Potential impact: Administration of these enzyme inhibitors decreases the peripheral conversion of T4 to T3, leading to decreased T3 levels. However, serum T4 levels are usually normal but may occasionally be slightly increased.
Drug or Drug Class | Effect
Beta-adrenergic antagonists (e.g., Propranolol >160 mg/day) | In patients treated with large doses of propranolol (>160 mg/day), T3 and T4 levels change slightly, TSH levels remain normal, and patients are clinically euthyroid. It should be noted that actions of particular beta-adrenergic antagonists may be impaired when the hypothyroid patient is converted to the euthyroid state.
Glucocorticoids (e.g., Dexamethasone ≥4 mg/day) | Short-term administration of large doses of glucocorticoids may decrease serum T3 concentrations by 30% with minimal change in serum T4 levels. However, long-term glucocorticoid therapy may result in slightly decreased T3 and T4 levels due to decreased TBG production (see above).
Other: Amiodarone) | Amiodarone inhibits peripheral conversion of levothyroxine (T4) to triiodothyronine (T3) and may cause isolated biochemical changes (increase in serum free-T4, and decreased or normal free-T3) in clinically euthyroid patients.

7.2 Antidiabetic Therapy

Addition of LEVOXYL therapy in patients with diabetes mellitus may worsen glycemic control and result in increased antidiabetic agent or insulin requirements. Carefully monitor glycemic control, especially when LEVOXYL is started, changed, or discontinued [see Warnings and Precautions (5.5)].

7.3 Oral Anticoagulants

LEVOXYL increases the response to oral anticoagulant therapy. Therefore, a decrease in the dose of anticoagulant may be warranted with correction of the hypothyroid state or when the LEVOXYL dose is increased. Closely monitor coagulation tests to permit appropriate and timely dosage adjustments.

7.4 Digitalis Glycosides

LEVOXYL may reduce the therapeutic effects of digitalis glycosides. Serum digitalis glycoside levels may be decreased when a hypothyroid patient becomes euthyroid, necessitating an increase in the dose of digitalis glycosides.

7.5 Antidepressant Therapy

Concurrent use of tricyclic (e.g., amitriptyline) or tetracyclic (e.g., maprotiline) antidepressants and LEVOXYL may increase the therapeutic and toxic effects of both drugs, possibly due to increased receptor sensitivity to catecholamines. Toxic effects may include increased risk of cardiac arrhythmias and central nervous system stimulation. LEVOXYL may accelerate the onset of action of tricyclics. Administration of sertraline in patients stabilized on LEVOXYL may result in increased LEVOXYL requirements.

7.6 Ketamine

Concurrent use of ketamine and LEVOXYL may produce marked hypertension and tachycardia. Closely monitor blood pressure and heart rate in these patients.

7.7 Sympathomimetics

Concurrent use of sympathomimetics and LEVOXYL may increase the effects of sympathomimetics or thyroid hormone. Thyroid hormones may increase the risk of coronary insufficiency when sympathomimetic agents are administered to patients with coronary artery disease.

7.8 Tyrosine-Kinase Inhibitors

Concurrent use of tyrosine-kinase inhibitors such as imatinib may cause hypothyroidism. Closely monitor TSH levels in such patients.

7.9 Drug-Food Interactions

Consumption of certain foods may affect LEVOXYL absorption thereby necessitating adjustments in dosing [see Dosage and Administration (2.1)]. Soybean flour (infant formula), cotton seed meal, walnuts, and dietary fiber may bind and decrease the absorption of LEVOXYL from the GI tract. Grapefruit juice may delay the absorption of levothyroxine and reduce its bioavailability.

7.10 Drug-Laboratory Test Interactions

Consider changes in TBG concentration when interpreting T4 and T3 values. Measure and evaluate unbound (free) hormone and/or determine the free T4 index (FT4I) in this circumstance. Pregnancy, infectious hepatitis, estrogens, estrogen-containing oral contraceptives, and acute intermittent porphyria increase TBG concentrations. Nephrosis, severe hypoproteinemia, severe liver disease, acromegaly, androgens, and corticosteroids decrease TBG concentration. Familial hyper- or hypo-thyroxine-binding globulinemias have been described, with the incidence of TBG deficiency approximating 1 in 9000.

8 USE IN SPECIFIC POPULATIONS

8.1 Pregnancy

Risk Summary

Experience with levothyroxine use in pregnant women, including data from post-marketing studies, have not reported increased rates of major birth defects or miscarriages (see Data). There are risks to the mother and fetus associated with untreated hypothyroidism in pregnancy. Since thyroid-stimulating hormone (TSH) levels may increase during pregnancy, TSH should be monitored and LEVOXYL dosage adjusted during pregnancy (see Clinical Considerations). There are no animal studies conducted with levothyroxine during pregnancy. LEVOXYL should not be discontinued during pregnancy and hypothyroidism diagnosed during pregnancy should be promptly treated.

The estimated background risk of major birth defects and miscarriage for the indicated population is unknown. In the U.S. general population, the estimated background risk of major birth defects and miscarriage in clinically recognized pregnancies is 2 to 4% and 15 to 20%, respectively.

Clinical Considerations

Disease-Associated Maternal and/or Embryo/Fetal Risk

Maternal hypothyroidism during pregnancy is associated with a higher rate of complications, including spontaneous abortion, gestational hypertension, pre-eclampsia, stillbirth, and premature delivery. Untreated maternal hypothyroidism may have an adverse effect on fetal neurocognitive development.

Dose Adjustments During Pregnancy and the Postpartum Period

Pregnancy may increase LEVOXYL requirements. Serum TSH level should be monitored and the LEVOXYL dosage adjusted during pregnancy. Since postpartum TSH levels are similar to preconception values, the LEVOXYL dosage should return to the pre-pregnancy dose immediately after delivery [see Dosage and Administration (2.3)].

Data

Human Data

Levothyroxine is approved for use as a replacement therapy for hypothyroidism. There is a long experience of levothyroxine use in pregnant women, including data from post-marketing studies that have not reported increased rates of fetal malformations, miscarriages or other adverse maternal or fetal outcomes associated with levothyroxine use in pregnant women.

8.2 Lactation

Risk Summary

Limited published studies report that levothyroxine is present in human milk. However, there is insufficient information to determine the effects of levothyroxine on the breastfed infant and no available information on the effects of levothyroxine on milk production. Adequate levothyroxine treatment during lactation may normalize milk production in hypothyroid lactating mothers. The developmental and health benefits of breastfeeding should be considered along with the mother's clinical need for LEVOXYL and any potential adverse effects on the breastfed infant from LEVOXYL or from the underlying maternal condition.

8.4 Pediatric Use

The initial dose of LEVOXYL varies with age and body weight. Dosing adjustments are based on an assessment of the individual patient's clinical and laboratory parameters [see Dosage and Administration (2.3, 2.4)].

In children in whom a diagnosis of permanent hypothyroidism has not been established, discontinue LEVOXYL for a trial period, but only after the child is at least 3 years of age. Obtain serum T4 and TSH levels at the end of the trial period, and use laboratory test results and clinical assessments to guide diagnosis and treatment, if warranted.

Congenital Hypothyroidism [see Dosage and Administration (2.3, 2.4)]

Rapid restoration of normal serum T4 concentrations is essential for preventing the adverse effects of congenital hypothyroidism on intellectual development as well as on overall physical growth and maturation. Therefore, initiate LEVOXYL therapy immediately upon diagnosis. Levothyroxine is generally continued for life in these patients.

Closely monitor infants during the first 2 weeks of LEVOXYL therapy for cardiac overload, arrhythmias, and aspiration from avid suckling.

Closely monitor patients to avoid undertreatment or overtreatment. Undertreatment may have deleterious effects on intellectual development and linear growth. Overtreatment is associated with craniosynostosis in infants, may adversely affect the tempo of brain maturation, and may accelerate the bone age and result in premature epiphyseal closure and compromised adult stature.

Acquired Hypothyroidism in Pediatric Patients

Closely monitor patients to avoid undertreatment and overtreatment. Undertreatment may result in poor school performance due to impaired concentration and slowed mentation and in reduced adult height. Overtreatment may accelerate the bone age and result in premature epiphyseal closure and compromised adult stature.

Treated children may manifest a period of catch-up growth, which may be adequate in some cases to normalize adult height. In children with severe or prolonged hypothyroidism, catch-up growth may not be adequate to normalize adult height.

8.5 Geriatric Use

Because of the increased prevalence of cardiovascular disease among the elderly, initiate LEVOXYL at less than the full replacement dose [see Dosage and Administration (2.3), Warnings and Precautions (5.1)]. Atrial arrhythmias can occur in elderly patients. Atrial fibrillation is the most common of the arrhythmias observed with levothyroxine overtreatment in the elderly.

10 OVERDOSAGE

The signs and symptoms of overdosage are those of hyperthyroidism [see Warnings and Precautions (5.4), Adverse Reactions (6)]. In addition, confusion and disorientation may occur. Cerebral embolism, shock, coma, and death have been reported. Seizures occurred in a 3-year-old child ingesting 3.6 mg of levothyroxine. Symptoms may not necessarily be evident or may not appear until several days after ingestion of levothyroxine sodium.

Reduce the LEVOXYL dose or temporarily discontinued if signs or symptoms of overdosage occur. Initiate appropriate supportive treatment as dictated by the patient's medical status.

For current information on the management of poisoning or overdosage, contact the National Poison Control Center at 1-800-222-1222 or www.poison.org.

11 DESCRIPTION

LEVOXYL contains the active ingredient, levothyroxine, asynthetic crystalline levothyroxine (T4) in sodium salt form. It is chemically designated as L-3,3',5,5'-tetraiodothyronine monosodium hydrate. Synthetic T4 is identical in chemical structure to the T4 produced in the human thyroid gland. Levothyroxine sodium has an empirical formula of C15H10I4N NaO4 ∙ H2O, molecular weight of 798.85 g/mol (anhydrous), and structural formula as shown:

LEVOXYL tablets for oral administration are supplied in the following strengths: 25 mcg, 50 mcg, 75 mcg, 88 mcg, 100 mcg, 112 mcg, 125 mcg, 137 mcg, 150 mcg, 175 mcg, and 200 mcg.

Inactive Ingredients

Calcium sulfate dihydrate, croscarmellose sodium, magnesium stearate, microcrystalline cellulose, and sodium bicarbonate. The following are the coloring additives per tablet strength:

Strength (mcg) | Color additive(s)
25 | FD&C Yellow No. 6 Aluminum Lake
50 | None
75 | FD&C Blue No. 1 Aluminum Lake, D&C Red No. 30 Aluminum Lake
88 | FD&C Yellow No. 6 Aluminum Lake, FD&C Blue No. 1 Aluminum Lake, D&C Yellow No. 10 Aluminum Lake
100 | FD&C Yellow No. 6 Aluminum Lake, D&C Yellow No. 10 Aluminum Lake
112 | FD&C Yellow No. 6 Aluminum Lake, FD&C Red No. 40 Aluminum Lake, D&C Red No. 30 Aluminum Lake
125 | FD&C Red No. 40 Aluminum Lake, D&C Yellow No. 10 Aluminum Lake
137 | FD&C Blue No. 1 Aluminum Lake
150 | FD&C Blue No. 1 Aluminum Lake, D&C Red No. 30 Aluminum Lake
175 | FD&C Blue No. 1 Aluminum Lake, D&C Yellow No. 10 Aluminum Lake
200 | D&C Red No. 30 Aluminum Lake, D&C Yellow No. 10 Aluminum Lake

12 CLINICAL PHARMACOLOGY

12.1 Mechanism of Action

Thyroid hormones exert their physiologic actions through control of DNA transcription and protein synthesis. Triiodothyronine (T3) and L-thyroxine (T4) diffuse into the cell nucleus and bind to thyroid receptor proteins attached to DNA. This hormone nuclear receptor complex activates gene transcription and synthesis of messenger RNA and cytoplasmic proteins.

The physiological actions of thyroid hormones are produced predominantly by T3, the majority of which (approximately 80%) is derived from T4 by deiodination in peripheral tissues.

12.2 Pharmacodynamics

Oral levothyroxine sodium is a synthetic T4 hormone that exerts the same physiologic effect as endogenous T4, thereby maintaining normal T4 levels when a deficiency is present.

12.3 Pharmacokinetics

Absorption

Absorption of orally administered T4 from the gastrointestinal tract ranges from 40% to 80%. The majority of the levothyroxine dose is absorbed from the jejunum and upper ileum. The relative bioavailability of LEVOXYL tablets, compared to an equal nominal dose of oral levothyroxine sodium solution, is approximately 95% to 98%. T4 absorption is increased by fasting, and decreased in malabsorption syndromes and by certain foods such as soybeans. Dietary fiber decreases bioavailability of T4. Absorption may also decrease with age. In addition, many drugs and foods affect T4 absorption [see Drug Interactions (7)].

Distribution

Circulating thyroid hormones are greater than 99% bound to plasma proteins, including thyroxine-binding globulin (TBG), thyroxine-binding prealbumin (TBPA), and thyroxine-binding albumin (TBA), whose capacities and affinities vary for each hormone. The higher affinity of both TBG and TBPA for T4 partially explains the higher serum levels, slower metabolic clearance, and longer half-life of T4 compared to T3. Protein-bound thyroid hormones exist in reverse equilibrium with small amounts of free hormone. Only unbound hormone is metabolically active. Many drugs and physiologic conditions affect the binding of thyroid hormones to serum proteins [see Drug Interactions (7)]. Thyroid hormones do not readily cross the placental barrier [see Use in Specific Populations (8.1)].

Elimination

Metabolism

T4 is slowly eliminated (Table 7). The major pathway of thyroid hormone metabolism is through sequential deiodination. Approximately 80 % of circulating T3 is derived from peripheral T4 by monodeiodination. The liver is the major site of degradation for both T4 and T3, with T4 deiodination also occurring at a number of additional sites, including the kidney and other tissues. Approximately 80% of the daily dose of T4 is deiodinated to yield equal amounts of T3 and reverse T3 (rT3). T3 and rT3 are further deiodinated to diiodothyronine. Thyroid hormones are also metabolized via conjugation with glucuronides and sulfates and excreted directly into the bile and gut where they undergo enterohepatic recirculation.

Excretion

Thyroid hormones are primarily eliminated by the kidneys. A portion of the conjugated hormone reaches the colon unchanged and is eliminated in the feces. Approximately 20% of T4 is eliminated in the stool. Urinary excretion of T4 decreases with age.

Table 7: Pharmacokinetic Parameters of Thyroid Hormones in Euthyroid Patients
Hormone | Ratio in Thyroglobulin | Biologic Potency | t½ (days) | Protein Binding (%) [Includes TBG, TBPA, and TBA]
Levothyroxine (T4) | 10–20 | 1 | 6–7 [3 to 4 days in hyperthyroidism, 9 to 10 days in hypothyroidism] | 99.96
Liothyronine (T3) | 1 | 4 | ≤2 | 99.5

13 NONCLINICAL TOXICOLOGY

13.1 Carcinogenesis, Mutagenesis, Impairment of Fertility

Animal studies have not been performed to evaluate the carcinogenic potential, mutagenic potential or effects on fertility of levothyroxine sodium.

16 HOW SUPPLIED/STORAGE AND HANDLING

LEVOXYL (levothyroxine sodium) tablets are oval, color-coded and, potency marked available as follows:

Strength (mcg) | Color | Tablet Markings | NDC - bottles of 100 | NDC - bottles of 1000
25 | Orange | 25 | 60793-850-01 | 60793-850-10
50 | White | 50 | 60793-851-01 | 60793-851-10
75 | Purple | 75 | 60793-852-01 | 60793-852-10
88 | Olive | 88 | 60793-853-01 | 60793-853-10
100 | Yellow | 100 | 60793-854-01 | 60793-854-10
112 | Rose | 112 | 60793-855-01 | 60793-855-10
125 | Light Brown | 125 | 60793-856-01 | 60793-856-10
137 | Dark Blue | 137 | 60793-857-01 | 60793-857-10
150 | Blue | 150 | 60793-858-01 | 60793-858-10
175 | Turquoise | 175 | 60793-859-01 | 60793-859-10
200 | Pink | 200 | 60793-860-01 | 60793-860-10

STORAGE CONDITIONS

Store between 68°F–77°F (20°C–25°C) with excursions permitted between 59°F–86°F (15°C–30°C). Store LEVOXYL away from heat, moisture, and light.

17 PATIENT COUNSELING INFORMATION

Advise the patient to read the FDA-approved patient labeling (Patient Information).

Dosing and Administration

- Instruct patients to take LEVOXYL only as directed by their healthcare provider.
- Instruct patients to take LEVOXYL as a single dose, preferably on an empty stomach, one-half to one hour before breakfast with a full glass of water to avoid choking or gagging.
- Inform patients that agents such as iron and calcium supplements and antacids can decrease the absorption of levothyroxine. Instruct patients not to take LEVOXYL tablets within 4 hours of these agents.
- Instruct patients to notify their healthcare provider should they become pregnant or breastfeeding or are thinking of becoming pregnant, while taking LEVOXYL.

Important Information

- Inform patients that it may take several weeks before they notice an improvement in symptoms.
- Inform patients that the levothyroxine in LEVOXYL is intended to replace a hormone that is normally produced by the thyroid gland. Generally, replacement therapy is to be taken for life.
- Inform patients that LEVOXYL should not be used as a primary or adjunctive therapy in a weight control program.
- Instruct patients to notify their healthcare provider if they are taking any other medications, including prescription and over-the-counter preparations.
- Instruct patients to notify their healthcare provider of any other medical conditions you may have, particularly heart disease, diabetes, clotting disorders, and adrenal or pituitary gland problems as the dose of medications used to control these other conditions may need to be adjusted while taking LEVOXYL. If they have diabetes, instruct patients to monitor their blood and/or urinary glucose levels as directed by their physician and immediately report any changes to their physician. If patients are taking anticoagulants, their clotting status should be checked frequently.
- Instruct patients to notify their physician or dentist if they are taking LEVOXYL prior to any surgery.

Adverse Reactions

- Instruct patients to notify their healthcare provider if they experience any of the following symptoms: rapid or irregular heartbeat, chest pain, shortness of breath, leg cramps, headache, nervousness, irritability, sleeplessness, tremors, change in appetite, weight gain or loss, vomiting, diarrhea, excessive sweating, heat intolerance, fever, changes in menstrual periods, hives or skin rash, or any other unusual medical event.
- Inform patients that partial hair loss may occur rarely during the first few months of LEVOXYL therapy; this is usually temporary.

This product's label may have been updated. For the current prescribing information, please visit www.pfizer.com.

LAB-0709-2.0

Patient Information
LEVOXYL® (Lev-OX-il)
(levothyroxine sodium)
tablets, for oral use

What is the most important information I should know about LEVOXYL?

- Do not use LEVOXYL to treat weight problems or weight loss.
- Do not take more LEVOXYL than your healthcare provider prescribes for you to take. Over dosage or taking too much LEVOXYL may cause life-threatening side effects or death.

What is LEVOXYL?

LEVOXYL is a prescription medicine that contains a hormone called levothyroxine, which is similar to the hormone produced by your thyroid gland. LEVOXYL is used to treat children and adults:

- to replace or give extra levothyroxine in people whose thyroid does not produce enough of this hormone.
- who need surgery and radioiodine therapy to manage a type of thyroid cancer called well-differentiated thyroid cancer.

LEVOXYL should not be used to treat people who are recovering from swelling of the thyroid gland (thyroiditis) and whose bodies do not produce enough levothyroxine for a short time.

Do not use LEVOXYL if your adrenal glands are not working well and you have not been treated for this problem.

Before you take LEVOXYL, tell your healthcare provider about all of your medical conditions, including if you:

- have or had heart problems.
- have or had thyroid nodules.
- have adrenal or pituitary gland problems.
- have any food or drug allergies.
- have a low red blood cell count (anemia).
- have diabetes.
- have weak bones (osteoporosis).
- have or had a history of blood clotting problems.
- have recently received radiation therapy with iodine (such as I-131).
- are pregnant or plan to become pregnant. Your healthcare provider may need to increase your LEVOXYL while you are pregnant.

Tell your healthcare provider about all the medicines you take, including prescription and over-the-counter medicines, vitamins and herbal supplements. LEVOXYL may affect the way other medicines work, and other medicines may affect how LEVOXYL works. You can ask your healthcare provider or pharmacist for a list of medicines that interact with LEVOXYL.

Tell every healthcare provider including your dentist who treats you that you are taking LEVOXYL before any surgery.

How should I take LEVOXYL?

- Take LEVOXYL exactly as your healthcare provider tells you to take it.
- Your healthcare provider will tell you how much LEVOXYL to take each day.
- Take your dose of LEVOXYL on an empty stomach, at least 30 minutes to 1 hour before breakfast with a full glass of water to avoid choking or gagging.
- Giving LEVOXYL to infants and children who cannot swallow tablets:
  - Crush the tablet.
  - Place the freshly crushed tablet in a small amount (5 mL to 10 mL or 1 teaspoon to 2 teaspoons) of water.
  - Immediately give the medicine by spoon or dropper.
  - Do not store the mixed medicine. Do not give in foods that decrease the absorption of LEVOXYL, such as soybean-based infant formula.
- Your healthcare provider may change your dose if needed.
- Certain medicines can interfere with how LEVOXYL is absorbed by your body. Take or give LEVOXYL:
  - at least 4 hours before or after medicines that contain calcium carbonate or iron (ferrous sulfate).
  - at least 4 hours before medicines that contain bile acid sequestrants or ion exchange resins.

Know the medicines that you take. Ask your healthcare provider or pharmacist for a list of these medicines, if you are not sure.

- Certain foods and drinks including soybean flour, cotton seed meal, walnuts, grapefruit juice and dietary fiber can affect your treatment and dose of LEVOXYL. Talk to your healthcare provider if you eat or drink these foods.
- Your healthcare provider should do certain blood tests while you are taking LEVOXYL and may change your daily dose of LEVOXYL as needed. You should not stop taking LEVOXYL or change your dose unless your healthcare provider tells you to.
- It may take weeks before you notice your symptoms getting better. Keep using this medicine even if you feel well.
- You may have to take medicine for the rest of your life to replace the thyroid hormone your body cannot produce.
- If you take too much LEVOXYL or overdose, call your healthcare provider or poison control center at 1-800-222-1222, or go to the nearest hospital emergency room right away.

What are the possible side effects of LEVOXYL?

LEVOXYL can cause serious side effects, including:

- heart problems. You may experience an increased heart rate, chest pain and irregular heartbeat. Your risk of developing heart problems may be greater if you are elderly, have heart problems, or if you take too much LEVOXYL. Your healthcare provider may reduce your dose or stop treatment with LEVOXYL for a while if you develop heart problems.
- worsening diabetic control. If you are a diabetic, it may be harder to control your blood sugar levels causing hyperglycemia while taking LEVOXYL. Check your blood sugar levels closely after starting, changing, or stopping treatment with LEVOXYL, and tell your healthcare provider if there are any changes. Your healthcare provider may have to change your diabetes treatment plan.
- weak or brittle bones. Your risk of developing weak or brittle bones may be greater if you are post-menopausal and are taking high doses of LEVOXYL for a long period.

The most common side effects of LEVOXYL include:

- irregular heartbeat
- chest pain
- shortness of breath
- leg cramps
- headache
- nervousness
- hives or skin rash

- irritability
- sleep problems (insomnia)
- tremors
- muscle weakness
- change in appetite
- weight loss

- vomiting
- diarrhea
- sweating a lot
- heat intolerance
- fever
- changes in menstrual period

Other side effects may include:

- partial hair loss during the first months of treatment with LEVOXYL. This usually lasts a short period of time.

These are not all the possible side effects of LEVOXYL. Call your doctor for medical advice about side effects. You may report side effects to FDA at 1-800-FDA-1088.

How do I store LEVOXYL?

- Store LEVOXYL at room temperature between 68°F to 77°F (20°C to 25°C).
- Store LEVOXYL away from heat, light and moisture.
- Keep LEVOXYL and all other medicines out of the reach of children.

General information about the safe and effective use LEVOXYL.

Medicines are sometimes prescribed for purposes other than those listed in a Patient Information leaflet. Do not use LEVOXYL for a condition for which it was not prescribed. Do not give your LEVOXYL to other people, even if they have the same symptoms that you have. It may harm them.

You can ask your healthcare provider or pharmacist for information about LEVOXYL that was written for health professionals.

What are the ingredients in LEVOXYL?

Active ingredient: levothyroxine sodium

Inactive ingredients: microcrystalline cellulose, croscarmellose sodium, magnesium stearate, calcium sulfate dihydrate, sodium bicarbonate, coloring additives.

Gluten content: This product is gluten-free.

This product's label may have been updated. For current full prescribing information, please visit www.pfizer.com.

LAB-0710-1.0
December 2018

For more information, go to www.levoxyl.com, or call 1-866-295-7600

This Patient Information has been approved by the U.S. Food and Drug Administration

Issued:Dec 2018

PRINCIPAL DISPLAY PANEL - 25 mcg Tablet Bottle Label

NDC 60793-850-01

Pfizer

Levoxyl®
(levothyroxine
sodium tablets, USP)
tablets

25 mcg

100 Tablets
Rx only

PRINCIPAL DISPLAY PANEL - 50 mcg Tablet Bottle Label

NDC 60793-851-01

Pfizer

Levoxyl®
(levothyroxine
sodium tablets, USP)
tablets

50 mcg

100 Tablets
Rx only

PRINCIPAL DISPLAY PANEL - 75 mcg Tablet Bottle Label

NDC 60793-852-01

Pfizer

Levoxyl®
(levothyroxine
sodium tablets, USP)
tablets

75 mcg

100 Tablets
Rx only

PRINCIPAL DISPLAY PANEL - 88 mcg Tablet Bottle Label

NDC 60793-853-01

Pfizer

Levoxyl®
(levothyroxine
sodium tablets, USP)
tablets

88 mcg

100 Tablets
Rx only

PRINCIPAL DISPLAY PANEL - 100 mcg Tablet Bottle Label

NDC 60793-854-01

Pfizer

Levoxyl®
(levothyroxine
sodium tablets, USP)
tablets

100 mcg

100 Tablets
Rx only

PRINCIPAL DISPLAY PANEL - 112 mcg Tablet Bottle Label

NDC 60793-855-01

Pfizer

Levoxyl®
(levothyroxine
sodium tablets, USP)
tablets

112 mcg

100 Tablets
Rx only

PRINCIPAL DISPLAY PANEL - 125 mcg Tablet Bottle Label

NDC 60793-856-01

Pfizer

Levoxyl®
(levothyroxine
sodium tablets, USP)
tablets

125 mcg

100 Tablets
Rx only

PRINCIPAL DISPLAY PANEL - 137 mcg Tablet Bottle Label

NDC 60793-857-01

Pfizer

Levoxyl®
(levothyroxine
sodium tablets, USP)
tablets

137 mcg

100 Tablets
Rx only

PRINCIPAL DISPLAY PANEL - 150 mcg Tablet Bottle Label

NDC 60793-858-01

Pfizer

Levoxyl®
(levothyroxine
sodium tablets, USP)
tablets

150 mcg

100 Tablets
Rx only

PRINCIPAL DISPLAY PANEL - 175 mcg Tablet Bottle Label

NDC 60793-859-01

Pfizer

Levoxyl®
(levothyroxine
sodium tablets, USP)
tablets

175 mcg

100 Tablets
Rx only

PRINCIPAL DISPLAY PANEL - 200 mcg Tablet Bottle Label

NDC 60793-860-01

Pfizer

Levoxyl®
(levothyroxine
sodium tablets, USP)
tablets

200 mcg

100 Tablets
Rx only